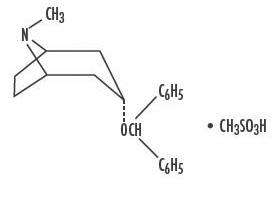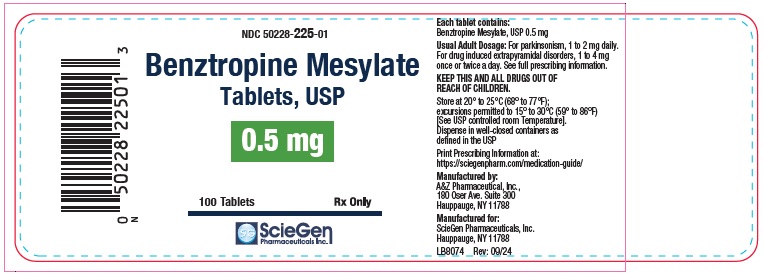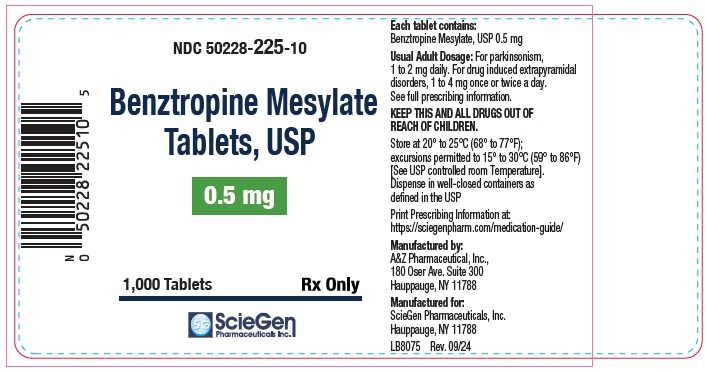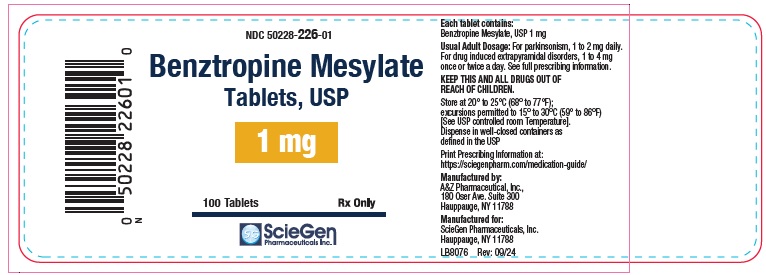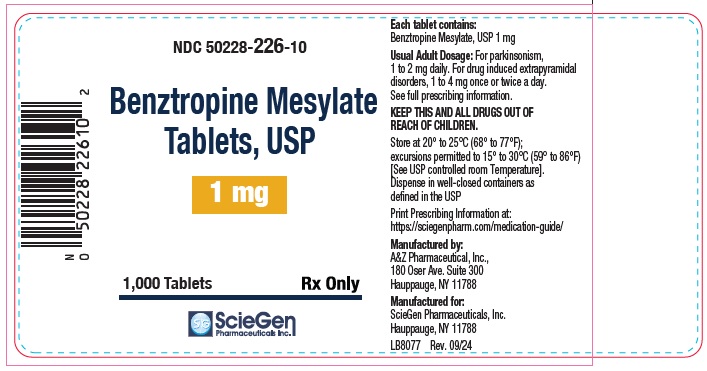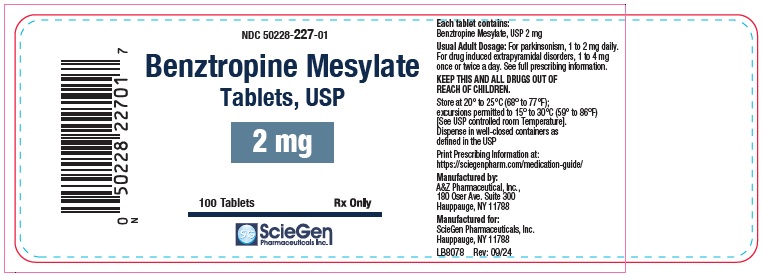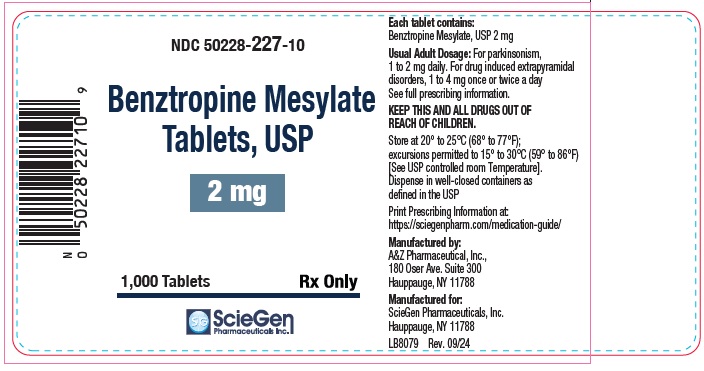 DRUG LABEL: Benztropine Mesylate
NDC: 50228-225 | Form: TABLET
Manufacturer: ScieGen Pharmaceuticals Inc
Category: prescription | Type: HUMAN PRESCRIPTION DRUG LABEL
Date: 20260109

ACTIVE INGREDIENTS: BENZTROPINE MESYLATE 0.5 mg/1 1
INACTIVE INGREDIENTS: ANHYDROUS LACTOSE; CROSCARMELLOSE SODIUM; FD&C RED NO. 40 ALUMINUM LAKE; FD&C YELLOW NO. 5 ALUMINUM LAKE; POVIDONE, UNSPECIFIED; MAGNESIUM STEARATE

BENZTROPINE MESYLATE Tablets, USP
Rx Only

DESCRIPTION

Benztropine mesylate is a synthetic compound containing structural features found in atropine and diphenhydramine.

It is designated chemically as 3α-(Diphenylmethoxy)-1αH, 5αH-tropane methanesulfonate. Its molecular formula is C21H25NO•CH4O3S, and its structural formula is:

Benztropine mesylate is a crystalline white powder, very soluble in water, and has a molecular weight of 403.54.

Each benztropine mesylate tablet USP for oral administration contains benztropine mesylate USP 0.5 mg, 1 mg or 2 mg.

Inactive ingredients: anhydrous lactose, croscarmellose sodium, FD&C Red #40 Aluminum Lake (2mg), FD&C Yellow #5 Aluminum Lake (1mg), povidone k-29/32, and magnesium stearate.

CLINICAL PHARMACOLOGY

Benztropine mesylate possesses both anticholinergic and antihistaminic effects, although only the former have been established as therapeutically significant in the management of parkinsonism.

In the isolated guinea pig ileum, the anticholinergic activity of this drug is about equal to that of atropine; however, when administered orally to unanesthetized cats, it is only about half as active as atropine.

In laboratory animals, its antihistaminic activity and duration of action approach those of pyrilamine maleate.

INDICATIONS AND USAGE

Benztropine mesylate tablets are indicated for use as an adjunct in the therapy of all forms of parkinsonism.

Useful also in the control of extrapyramidal disorders (except tardive dyskinesia – see PRECAUTIONS) due to neuroleptic drugs (e.g., phenothiazines).

CONTRAINDICATIONS

Hypersensitivity to benztropine mesylate tablets.
Because of its atropine-like side effects, this drug is contraindicated in pediatric patients under three years of age, and should be used with caution in older pediatric patients.

WARNINGS

Safe use in pregnancy has not been established.

Benztropine mesylate may impair mental and/or physical abilities required for performance of hazardous tasks, such as operating machinery or driving a motor vehicle.

When benztropine mesylate is given concomitantly with phenothiazines, haloperidol, or other drugs with anticholinergic or antidopaminergic activity, patients should be advised to report gastrointestinal complaints, fever or heat intolerance promptly. Paralytic ileus, hyperthermia and heat stroke, all of which have sometimes been fatal, have occurred in patients taking anticholinergic-type antiparkinsonism drugs, including benztropine mesylate, in combination with phenothiazines and/or tricyclic antidepressants.

Since benztropine mesylate contains structural features of atropine, it may produce anhidrosis. For this reason, it should be administered with caution during hot weather, especially when given concomitantly with other atropine-like drugs to the chronically ill, the alcoholic, those who have central nervous system disease, and those who do manual labor in a hot environment. Anhidrosis may occur more readily when some disturbance of sweating already exists. If there is evidence of anhidrosis, the possibility of hyperthermia should be considered. Dosage should be decreased at the discretion of the physician so that the ability to maintain body heat equilibrium by perspiration is not impaired. Severe anhidrosis and fatal hyperthermia have occurred.

PRECAUTIONS General

Since benztropine mesylate has cumulative action, continued supervision is advisable. Patients with a tendency to tachycardia and patients with prostatic hypertrophy should be observed closely during treatment.

Dysuria may occur, but rarely becomes a problem. Urinary retention has been reported with benztropine mesylate.

The drug may cause complaints of weakness and inability to move particular muscle groups, especially in large doses. For example, if the neck has been rigid and suddenly relaxes, it may feel weak, causing some concern. In this event, dosage adjustment is required.

Mental confusion and excitement may occur with large doses, or in susceptible patients. Visual hallucinations have been reported occasionally. Furthermore, in the treatment of extrapyramidal disorders due to neuroleptic drugs (e.g., phenothiazines), in patients with mental disorders, occasionally there may be intensification of mental symptoms. In such cases, antiparkinsonian drugs can precipitate a toxic psychosis. Patients with mental disorders should be kept under careful observation, especially at the beginning of treatment or if dosage is increased.

Tardive dyskinesia may appear in some patients on long-term therapy with phenothiazines and related agents, or may occur after therapy with these drugs has been discontinued. Antiparkinsonism agents do not alleviate the symptoms of tardive dyskinesia, and in some instances may aggravate them. Benztropine mesylate is not recommended for use in patients with tardive dyskinesia.

The physician should be aware of the possible occurrence of glaucoma. Although the drug does not appear to have any adverse effect on simple glaucoma, it probably should not be used in angle-closure glaucoma.

Drug Interactions

Antipsychotic drugs such as phenothiazines or haloperidol; tricyclic antidepressants (see WARNINGS).

Pediatric Use

Because of the atropine-like side effects, benztropine mesylate should be used with caution in pediatric patients over three years of age (see CONTRAINDICATIONS).

ADVERSE REACTIONS

The adverse reactions below, most of which are anticholinergic in nature, have been reported and within each category are listed in order of decreasing severity.

Cardiovascular
Tachycardia.

Digestive
Paralytic ileus, constipation, vomiting, nausea, dry mouth.

If dry mouth is so severe that there is difficulty in swallowing or speaking, or loss of appetite and weight, reduce dosage, or discontinue the drug temporarily.

Slight reduction in dosage may control nausea and still give sufficient relief of symptoms. Vomiting may be controlled by temporary discontinuation, followed by resumption at a lower dosage.

Nervous System
Toxic psychosis, including confusion, disorientation, memory impairment, visual hallucinations; exacerbation of pre-existing psychotic symptoms; nervousness; depression; listlessness; numbness of fingers.

Special Senses
Blurred vision, dilated pupils.

Urogenital
Urinary retention, dysuria.

Metabolic/Immune or Skin
Occasionally, an allergic reaction, e.g., skin rash, develops. If this cannot be controlled by dosage reduction, the medication should be discontinued.

Other
Heat stroke, hyperthermia, fever.

OVERDOSAGE

Manifestations- May be any of those seen in atropine poisoning or antihistamine overdosage; CNS depression, preceded or followed by stimulation; confusion; nervousness; listlessness; intensification of mental symptoms or toxic psychosis in patients with mental illness being treated with neuroleptic drugs (e.g., phenothiazines); hallucinations (especially visual); dizziness; muscle weakness; ataxia; dry mouth; mydriasis; blurred vision; palpitations; tachycardia; elevated blood pressure; nausea; vomiting; dysuria; numbness of fingers; dysphagia; allergic reactions, e.g., skin rash; headache; hot, dry, flushed skin; delirium; coma; shock; convulsions; respiratory arrest; anhidrosis; hyperthermia; glaucoma; constipation.

Treatment- Physostigmine salicylate, 1 to 2 mg, SC or IV, reportedly will reverse symptoms of anticholinergic intoxication. * A second injection may be given after 2 hours if required. Otherwise treatment is symptomatic and supportive. Induce emesis or perform gastric lavage (contraindicated in precomatose, convulsive, or psychotic states). Maintain respiration. A short-acting barbiturate may be used for CNS excitement, but with caution to avoid subsequent depression; supportive care for depression (avoid convulsant stimulants such as picrotoxin, pentylenetetrazol, or bemegride); artificial respiration for severe respiratory depression; a local miotic for mydriasis and cycloplegia; ice bags or other cold applications and alcohol sponges for hyperpyrexia, a vasopressor and fluids for circulatory collapse. Darken room for photophobia.

DOSAGE AND ADMINISTRATION

Benztropine mesylate tablets should be used when patients are able to take oral medication.

Because of cumulative action, therapy should be initiated with a low dose which is increased gradually at five- or six-day intervals to the smallest amount necessary for optimal relief. Increases should be made in increments of 0.5 mg, to a maximum of 6 mg, or until optimal results are obtained without excessive adverse reactions.

Postencephalitic and Idiopathic Parkinsonism - The usual daily dose is 1 to 2 mg, with a range of 0.5 to 6 mg orally.

As with any agent used in parkinsonism, dosage must be individualized according to age and weight, and the type of parkinsonism being treated. Generally, older patients, and thin patients cannot tolerate large doses. Most patients with postencephalitic parkinsonism need fairly large doses and tolerate them well. Patients with a poor mental outlook are usually poor candidates for therapy.

In idiopathic parkinsonism, therapy may be initiated with a single daily dose of 0.5 to 1 mg at bedtime. In some patients, this will be adequate; in others 4 to 6 mg a day may be required.

In postencephalitic parkinsonism, therapy may be initiated in most patients with 2 mg a day in one or more doses. In highly sensitive patients, therapy may be initiated with 0.5 mg at bedtime, and increased as necessary.

Some patients experience greatest relief by taking the entire dose at bedtime; others react more favorably to divided doses, two to four times a day. Frequently, one dose a day is sufficient, and divided doses may be unnecessary or undesirable.

The long duration of action of this drug makes it particularly suitable for bedtime medication when its effects may last throughout the night, enabling patients to turn in bed during the night more easily, and to rise in the morning.

When benztropine mesylate is started, do not terminate therapy with other antiparkinsonian agents abruptly. If the other agents are to be reduced or discontinued, it must be done gradually. Many patients obtain greatest relief with combination therapy.

Benztropine mesylate may be used concomitantly with Carbidopa-Levodopa, or with levodopa, in which case periodic dosage adjustment may be required in order to maintain optimum response.

Drug-Induced Extrapyramidal Disorders - In treating extrapyramidal disorders due to neuroleptic drugs (e.g., phenothiazines), the recommended dosage is 1 to 4 mg once or twice a day orally. Dosage must be individualized according to the need of the patient. Some patients require more than recommended; others do not need as much.

When extrapyramidal disorders develop soon after initiation of treatment with neuroleptic drugs (e.g., phenothiazines), they are likely to be transient. One to 2 mg of benztropine mesylate tablets two or three times a day usually provides relief within one or two days. After one or two weeks, the drug should be withdrawn to determine the continued need for it. If such disorders recur, benztropine mesylate can be reinstituted.

Certain drug-induced extrapyramidal disorders that develop slowly may not respond to benztropine mesylate.

HOW SUPPLIED

Benztropine Mesylate Tablets, USP are available as follows:

0.5 mg: White, biconvex, round tablets, debossed with “337” on one side, and plain with a bisect on the other side, in bottles of 100 (NDC 50228- 225-01), and 1,000 (NDC 50228-225-10).

1 mg: Light yellow, round, biconvex tablets debossed with “338” on one side and plain with a bisect on the other side, in bottles of 100 (NDC 50228-226-01) and 1,000 (NDC 50228-226-10).

2 mg: Light red, round, biconvex tablets debossed with “339” on one side and plain with a bisect on the other side, in bottles of 100 (NDC 50228-227-01) and 1,000 (NDC 50228-227-10).

Dispense in well-closed containers as defined in the USP.

Store at 20° to 25°C (68° to 77°F); excursions permitted to 15° to 30°C (59° to 86°F) [see USP Controlled Room Temperature].

Keep out of reach of children.
For more details please call 1-855-724-3436.

Dispense the Prescribing Information at:
https://sciegenpharm.com/medication-guide/

*Duvoisin, R.C.; Katz, R.J.; Amer. Med. Ass. 206: 1963–1965, Nov. 25, 1968.

Manufactured by:
A&Z Pharmaceutical, Inc.,
180 Oser Ave. Suite 300
Hauppauge, NY 11788

Manufactured for:
ScieGen Pharmaceuticals, Inc.
Hauppauge, NY 11788

Revised: 12/2025

LB8080

PRINCIPAL DISPLAY PANEL

NDC 50228-225-01

Benztropine Mesylate
Tablets, USP

0.5 mg

100 Tablets Rx Only

ScieGen
Pharmaceuticals Inc.

PRINCIPAL DISPLAY PANEL

NDC 50228-225-10

Benztropine Mesylate
Tablets, USP

0.5 mg

1,000 Tablets Rx Only

ScieGen
Pharmaceuticals Inc.

PRINCIPAL DISPLAY PANEL

NDC 50228-226-01

Benztropine Mesylate
Tablets, USP

1 mg

100 Tablets Rx Only

ScieGen
Pharmaceuticals Inc.

PRINCIPAL DISPLAY PANEL

NDC 50228-226-10

Benztropine Mesylate
Tablets, USP

1 mg

1,000 Tablets Rx Only

ScieGen
Pharmaceuticals Inc.

PRINCIPAL DISPLAY PANEL

NDC 50228-227-01

Benztropine Mesylate
Tablets, USP

2 mg

100 Tablets Rx Only

ScieGen
Pharmaceuticals Inc.

PRINCIPAL DISPLAY PANEL

NDC 50228-227-10

Benztropine Mesylate
Tablets, USP

2 mg

1,000 Tablets Rx Only

ScieGen
Pharmaceuticals Inc.